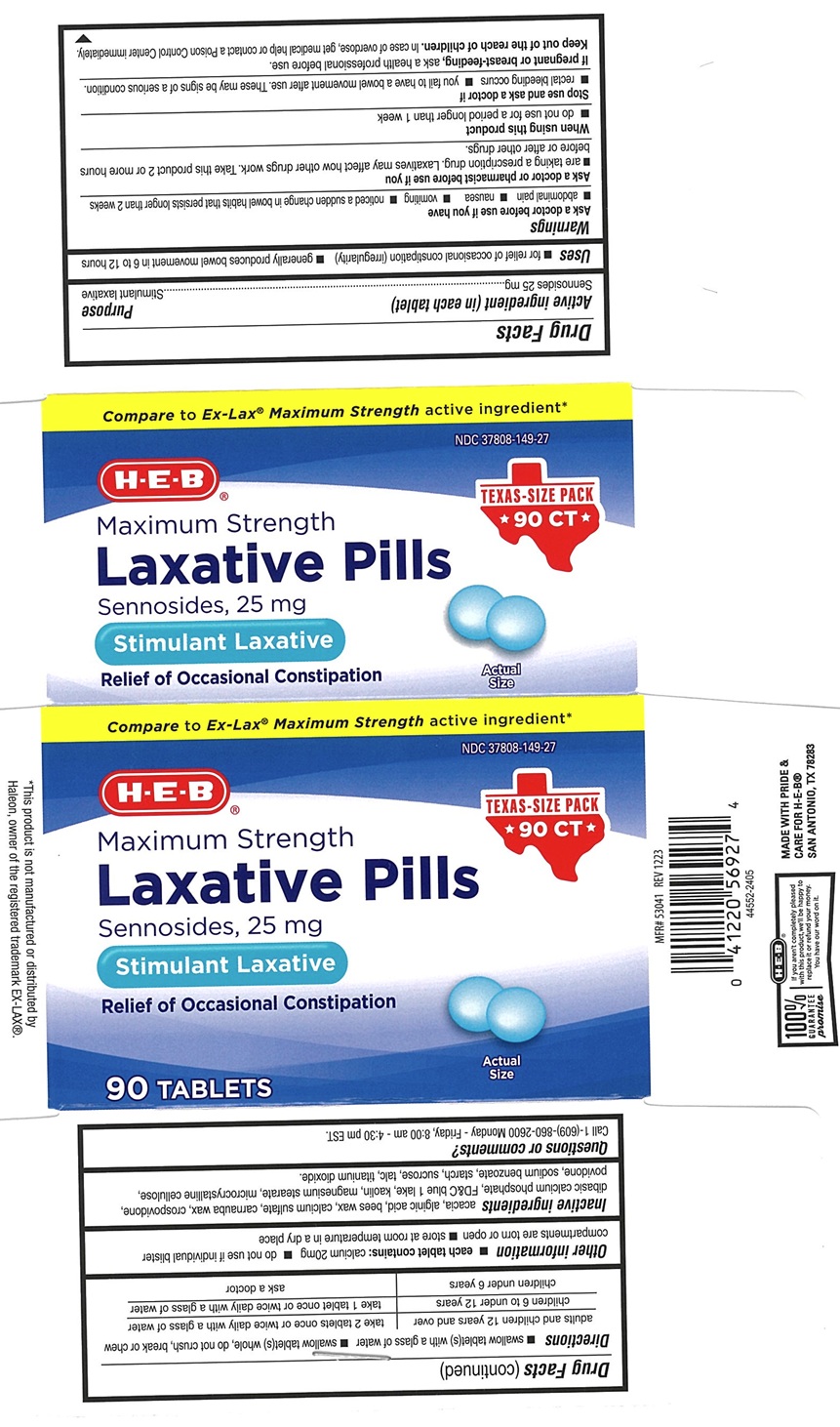 DRUG LABEL: HEB Maximum strength Laxative pills
NDC: 37808-149 | Form: TABLET
Manufacturer: H E B
Category: otc | Type: Human OTC Drug Label
Date: 20241226

ACTIVE INGREDIENTS: SENNOSIDES 25 mg/1 1
INACTIVE INGREDIENTS: ACACIA; ALGINIC ACID; CALCIUM SULFATE; YELLOW WAX; CARNAUBA WAX; CROSPOVIDONE, UNSPECIFIED; ANHYDROUS DIBASIC CALCIUM PHOSPHATE; FD&C BLUE NO. 1; KAOLIN; MAGNESIUM STEARATE; CELLULOSE, MICROCRYSTALLINE; POVIDONE, UNSPECIFIED; SODIUM BENZOATE; STARCH, CORN; SUCROSE; TALC; TITANIUM DIOXIDE

HEB Maximum Strength Laxative Pills

ACTIVE INGREDIENT(in each tablet)

Sennosides 25 mg

PURPOSE

Stimulant laxative

USE(S)

- for relief of occasional constipation (irregularity)
- generally produces bowel movement in 6 to 12 hours

WARNINGS

.

ASK A DOCTOR BEFORE USE IF YOU HAVE

- abdominal pain
- nausea
- vomiting
- noticed a sudden change in bowel habits that persists longer than 2 weeks

ASK A DOCTOR OR PHARMACIST BEFORE USE IF YOU

- are taking a prescription drug. Laxatives may affect how other drugs work. Take this product 2 or more hours before or after other drugs.

WHEN USING THIS PRODUCT

- do not use for a period longer than 1 week

STOP USE AND ASK A DOCTOR IF

- rectal bleeding occurs
- you fail to have a bowel movement after use. These may be signs of a serious condition.

IF PREGNANT OR BREASTFEEDING,

ask a health professional before use.

KEEP OUT OF REACH OF CHILDREN

In case of overdose, get medical help or contact a Poison Control Center immediately.

DIRECTIONS

- swallow tablet(s) with a glass of water
- swallow tablet(s) whole, do not crush, break or chew

adults and children 12 years and over | take 2 tablets once or twice daily with a glass of water
children 6 to under 12 years | take 1 tablet once or twice daily with a glass of water
children under 6 years | ask a doctor

OTHER INFORMATION

- each tablet contains: calcium 200 mg
- do not use if individual blister compartments are torn or open
- store at room temperature in a dry place

INACTIVE INGREDIENT SECTION

acacia, alginic acid, bees wax, calcium sulfate, carnauba wax, crospovidone, dibasic calcium phosphate, FD&C blue 1 lake, kaolin, magnesium stearate, microcrystalline cellulose, povidone, sodium benzoate, starch, sucrose, talc, titanium dioxide.

PRINCIPAL DISPLAY PANEL

Compare to Ex-Lax® Maximum strength active ingredient*
NDC 37808-149-27
HEB
Maximum Strength
Laxative Pills
Sennosides, 25 mg
Stimulant Laxative
Relief of Occasional Constipation
90 Tablets